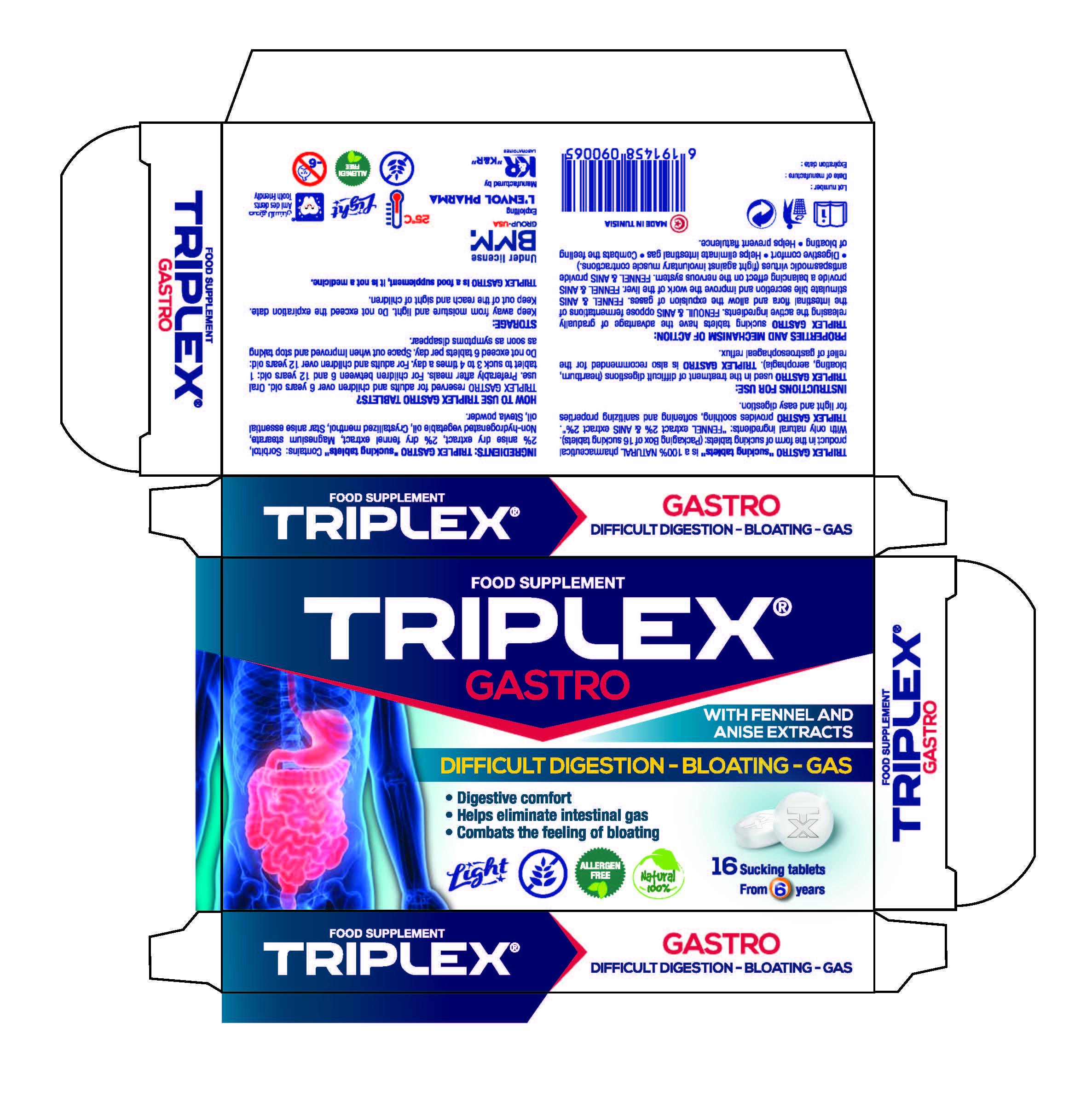 DRUG LABEL: Digestion-Bloating-Gas
NDC: 79394-000 | Form: PILL
Manufacturer: L'ENVOL PHARMA
Category: otc | Type: HUMAN OTC DRUG LABEL
Date: 20200722

ACTIVE INGREDIENTS: FENNEL 2 mg/100 mg; ANISE OIL 2 mg/100 mg
INACTIVE INGREDIENTS: STAR ANISE OIL; STEVIA LEAF; MENTHOL; MAGNESIUM STEARATE; HYDROGENATED AVOCADO OIL

Active Ingredient(s)

Anise Dry Extract 2%

Dry Fennel Extract 2%

Purpose

Light and Ease of Digestion

Use

Take 1 tablet 3-4 times a day when having issues with digestion

Warnings

No more than 6 tablets in a day.

Keep away from children

Do not use

- in children less than 2 months of age
- on open skin wounds

When using this product keep out of eyes, ears, and mouth. In case of contact with eyes, rinse eyes thoroughly with water.
Stop use and ask a doctor if irritation or rash occurs. These may be signs of a serious condition.
Keep out of reach of children. If swallowed, get medical help or contact a Poison Control Center right away.

Stop use and ask a doctor if irritation or rash occurs. These may be signs of a serious condition.

Keep out of reach of children. If any issues occur get medical help or contact a Poison Control Center right away.

Directions

- Take 1 tablet 3-4 times a day.
- Children under 12 years of age should not use product

Other information

- Store between 15-30C (59-86F)
- Avoid freezing and excessive heat above 40C (104F)

Inactive ingredients

Magnesium stearate, non-hydrogenated vegetable oil, Menthol, Star Asine essential oil,Stevia Powder

Package Label - Principal Display Panel

16 U NDC: 79394-000-01